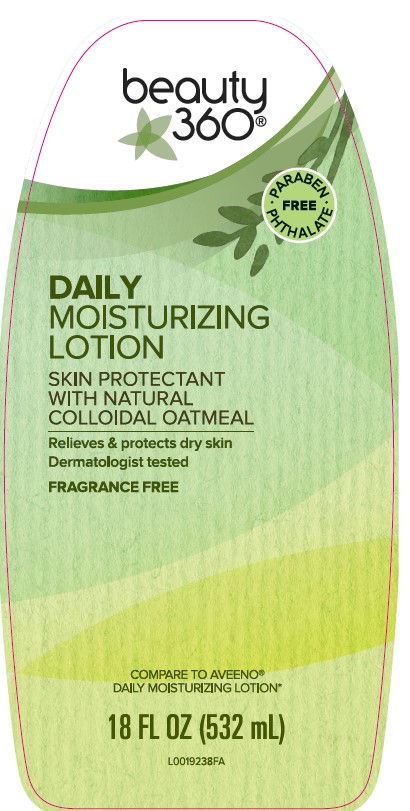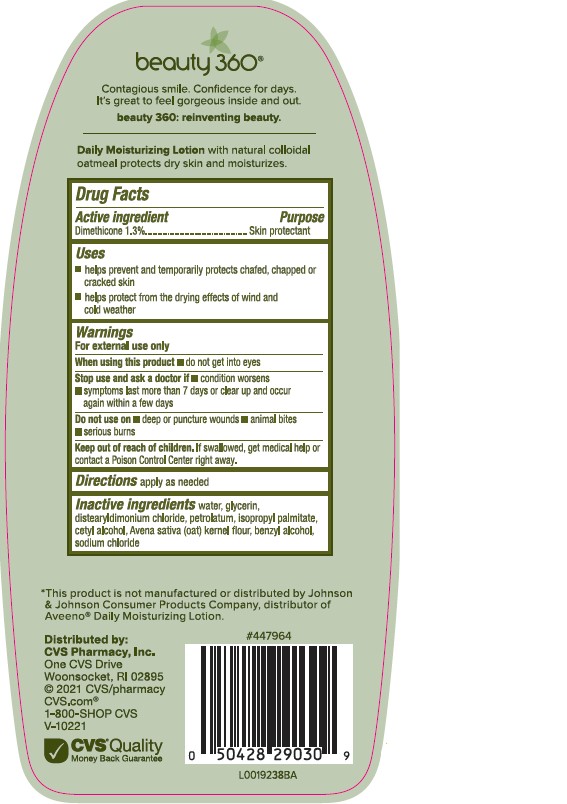 DRUG LABEL: Daily Moisturizing
NDC: 69842-771 | Form: LOTION
Manufacturer: CVS Pharmacy, Inc.
Category: otc | Type: HUMAN OTC DRUG LABEL
Date: 20260203

ACTIVE INGREDIENTS: DIMETHICONE 1.3 kg/100 mL
INACTIVE INGREDIENTS: WATER; GLYCERIN; DISTEARYLDIMONIUM CHLORIDE; PETROLATUM; ISOPROPYL PALMITATE; CETYL ALCOHOL; OATMEAL; BENZYL ALCOHOL; SODIUM CHLORIDE

CVS 619.003/619AC rev 2
Daily Moisturizing Lotion

Claims

beauty 360®

Contagious smile. Confidence for days.

It's great to feel gorgeous inside and out.

beauty 360: reinventing beauty.

Daily Moisturizing Lotionwith natural collodial oatmeal protects dry skin and moisturizes.

Active ingredient

Dimethicone 1.3%

Purpose

Skin Protectant

Uses

- helps prevent and temporarily protects chafed, chapped, cracked skin
- helps protect from the drying effects of wind and cold weather

Warnings

For external use only

When using this product

- keep out of eyes

Stop use and ask a doctor if

- condition worsens
- symptoms last more than 7 days or clear up and occur again within a few days

Do Not Use

- on deep or puncture wounds
- animal bites
- serious burns

Keep out of reach of children.

If swallowed, get medical help or contact a Poison Control Center right away.

Directions

apply as needed

Inactive ingredients

water, glycerin, distearyldimonium chloride, petrolatum, isopropyl palmitate, cetyl alcohol, Avena sativa (oat) kernel flour, benzyl alcohol, sodium chloride

Disclaimer

*This product is not manufactured or distributed by Johnson & Johnson Consumer Products Company, distributor of AveenoDaily Moisturizing Lotion.

ADVERSE REACTION

Distributed by:

CVS Pharmacy, Inc

One CVS Drive

Woonsocket, RI 02895

© 2021 CVS/pharmacy

CVS.com

1-800-SHOP CVS

V-10221

CVSQuality

Money Back Guarantee

principal display panel

beauty 360®

PARABEN - PHTHALATE FREE

DAILY MOISTURIZING LOTION

SKIN PROTECTANT

WITH NATURAL COLLOIDAL OATMEAL

Relieves & protects dry skin

Dermatologitst tested

FRAGRANCE FREE

COMPARE TO AVEENO®DAILY MOISTURIZING LOTION*

18 FL OZ (532 mL)